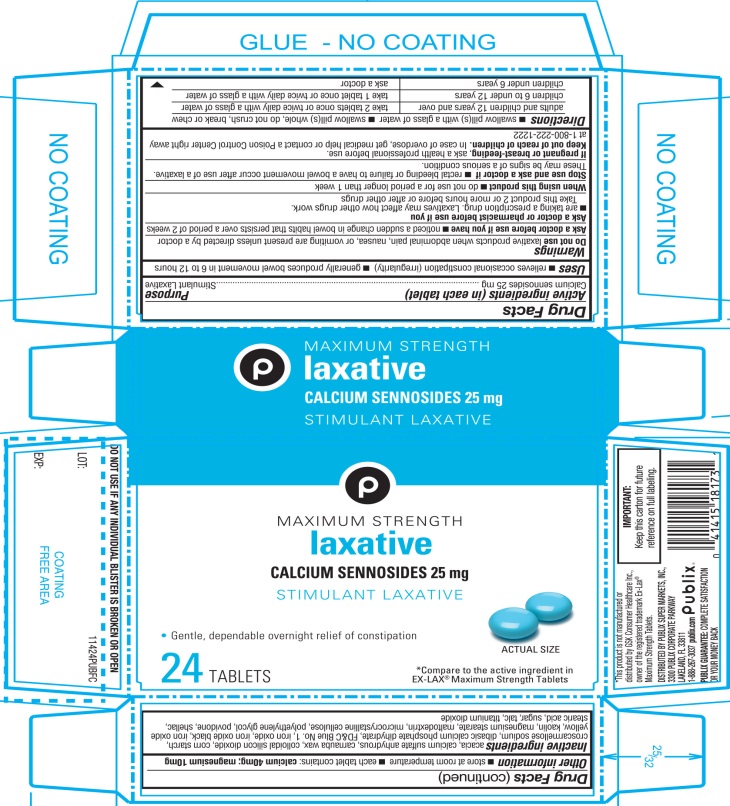 DRUG LABEL: Publix Laxative

NDC: 41415-114 | Form: TABLET
Manufacturer: PUBLIX SUPER MARKETS, INC
Category: otc | Type: HUMAN OTC DRUG LABEL
Date: 20251028

ACTIVE INGREDIENTS: SENNOSIDES A AND B 25 mg/1 1
INACTIVE INGREDIENTS: ACACIA; CALCIUM SULFATE ANHYDROUS; CARNAUBA WAX; SILICON DIOXIDE; STARCH, CORN; CROSCARMELLOSE SODIUM; DIBASIC CALCIUM PHOSPHATE DIHYDRATE; FD&C BLUE NO. 1; FERROSOFERRIC OXIDE; FERRIC OXIDE RED; FERRIC OXIDE YELLOW; KAOLIN; MAGNESIUM STEARATE; MALTODEXTRIN; MICROCRYSTALLINE CELLULOSE; POLYETHYLENE GLYCOL, UNSPECIFIED; POVIDONE, UNSPECIFIED; SHELLAC; STEARIC ACID; RAW SUGAR; TALC; TITANIUM DIOXIDE

Publix Maximum Laxative 24 Tablets

Active ingredient (in each tablet)

Calcium Sennosides 25 mg

Purpose

Stimulant laxative

Uses

- relieves occasional constipation (irregularity)
- generally produces bowel movement in 6 to 12 hours

Warnings

Do not use

laxative products when abdominal pain, nausea, or vomiting are present unless directed by a doctor.

Ask a doctor before use if you have

- noticed a sudden change in bowel habits that persists over a period of 2 weeks.

Ask a doctor or pharmacist before use if you are

- are taking a prescription drug. Laxatives may affect how other drugs work. Take this product 2 or more hours before or after other drugs.

When using this product,

- do not use for a period longer than 1 week.

Stop use and ask a doctor if

- rectal bleeding or failure to have a bowel movement occurs after use of a laxative.

These may be signs of a serious condition.

If pregnant or breast-feeding,

ask a health professional before use.

Keep out of reach of children.

In case of overdose, get medical help or contact a Poison Control Center right away at (1-800-222-1222).

Directions

- swallow pill(s) with a glass of water
- swallow pill(s) whole; do not crush, break, or chew

adults and children 12 years and over | take 2 tablets once or twice daily with a glass of water
children 6 to under 12 years | take1 tablet once or twice daily with a glass of water
children under 6 years | ask a doctor

Other information

- each tablet contains: calcium 40 mg, magnesium 10 mg
- store at room temperature

Inactive ingredients

acacia, calcium sulfate anhydrous, carnauba wax, colloidal silicon dioxide, corn starch, croscarmellose sodium, dibasic calcium phosphate dehydrate, FD&C Blue No. 1, iron oxide, iron oxide black, iron oxide yellow, kaolin, magnesium sterate, maltodextrin, microcrystalline cellulose, polyethylene glycol, povidone, shellac, stearic acid, sugar, talc, titanium dioxide.

Principal Display Panel

*Compare to the active ingredient in EX-LAX®Maximum Strength Tablets

Publix®

NDC# 41415-114-24

MAXIMUM STRENGTH
Laxative

CALCIUM SENNOSIDES USP 25 mg/
STIMULANT LAXATIVE

24TABLETS

TAMPER EVIDENT: DO NOT USE IF ANY INDIVIDUAL BLISTER IS BROKEN OR OPEN.

DISTRIBUTED BY PUBLIX SUPER MARKETS, INC.,

3300 PUBLIX CORPORATE PARKWAY

LAKELAND, FL 33811

1-888-267-3037 publix.com

PUBLIX GUARANTEE: COMPLETE SATISFACTION OR YOUR MONEY BACK